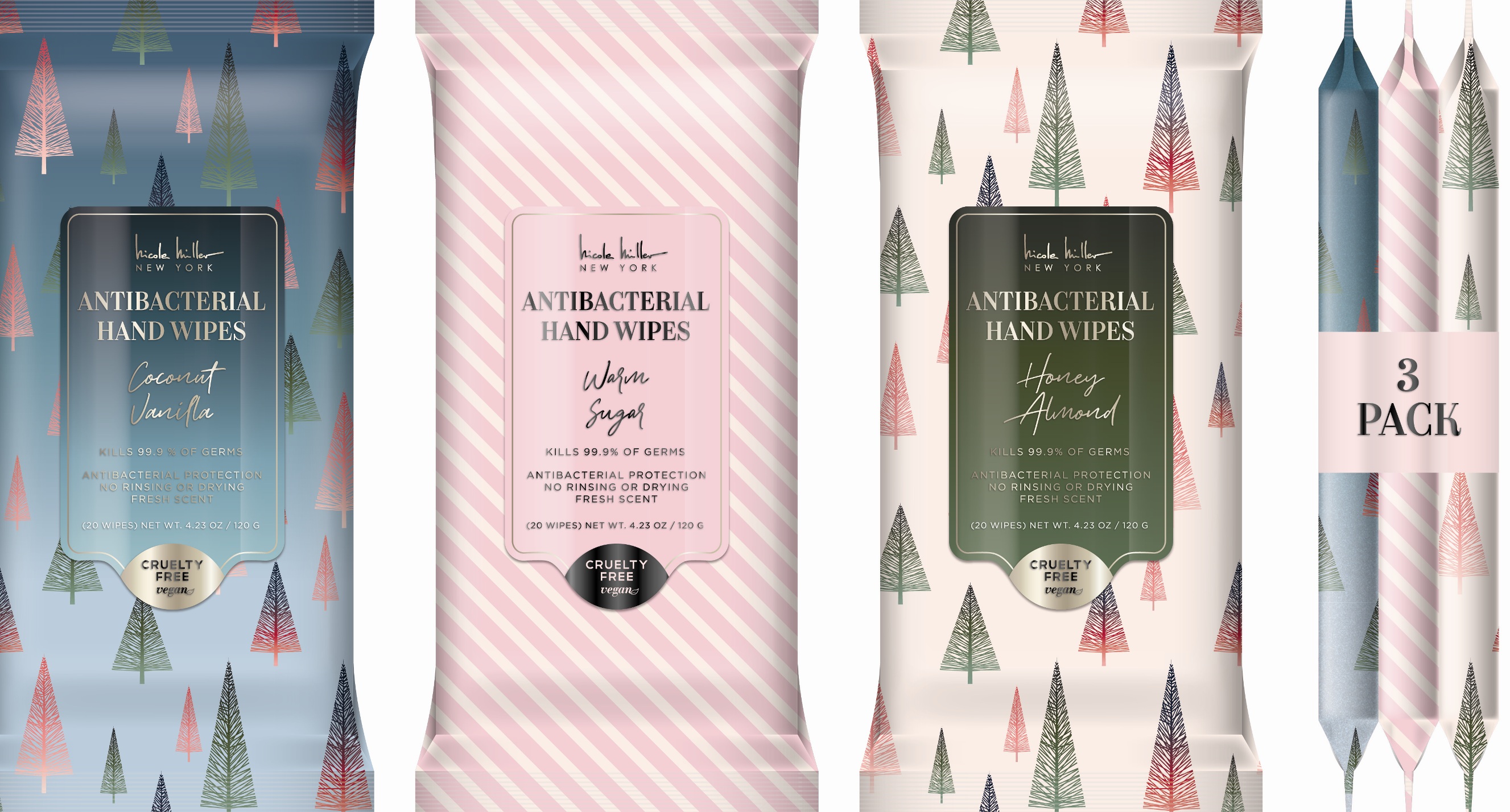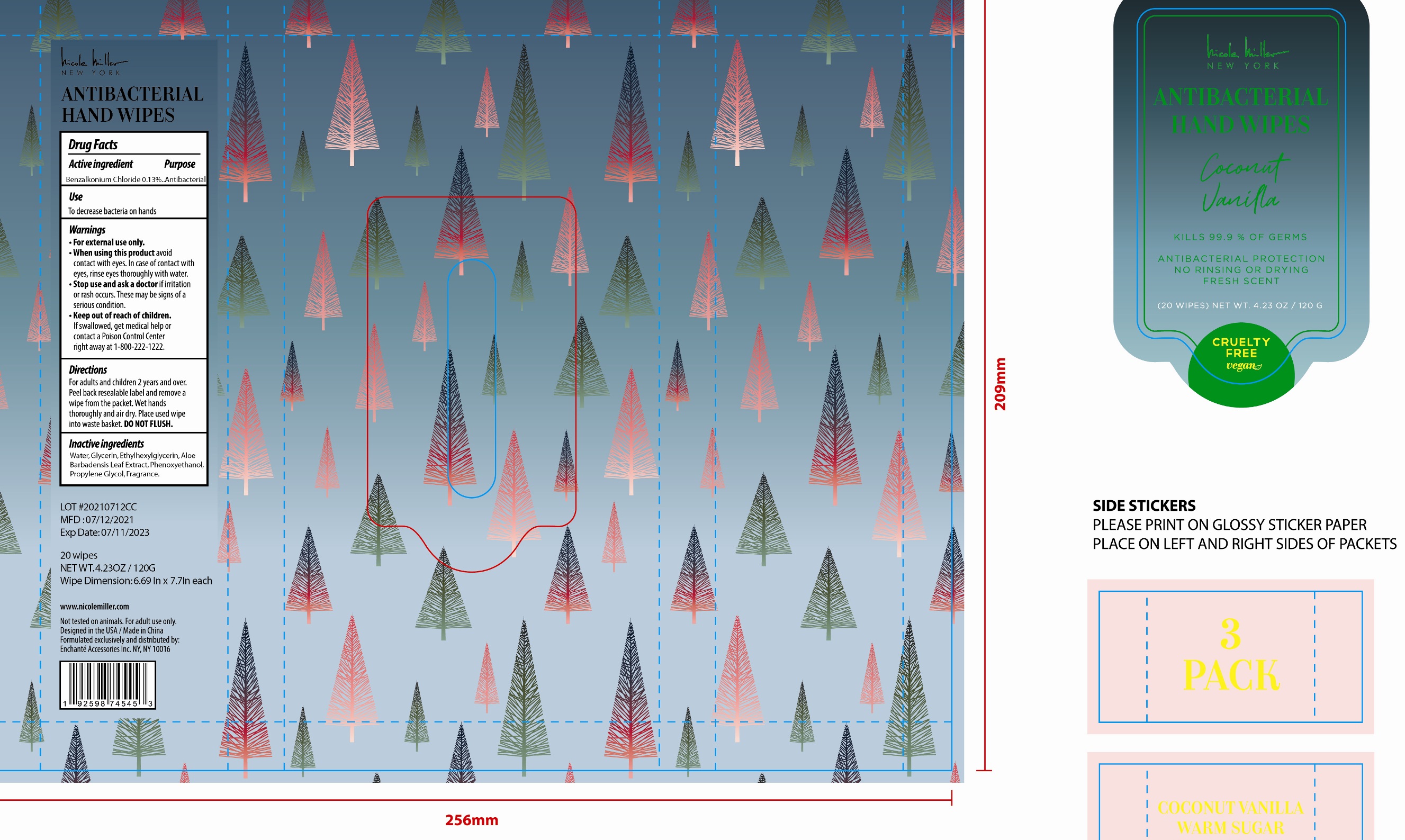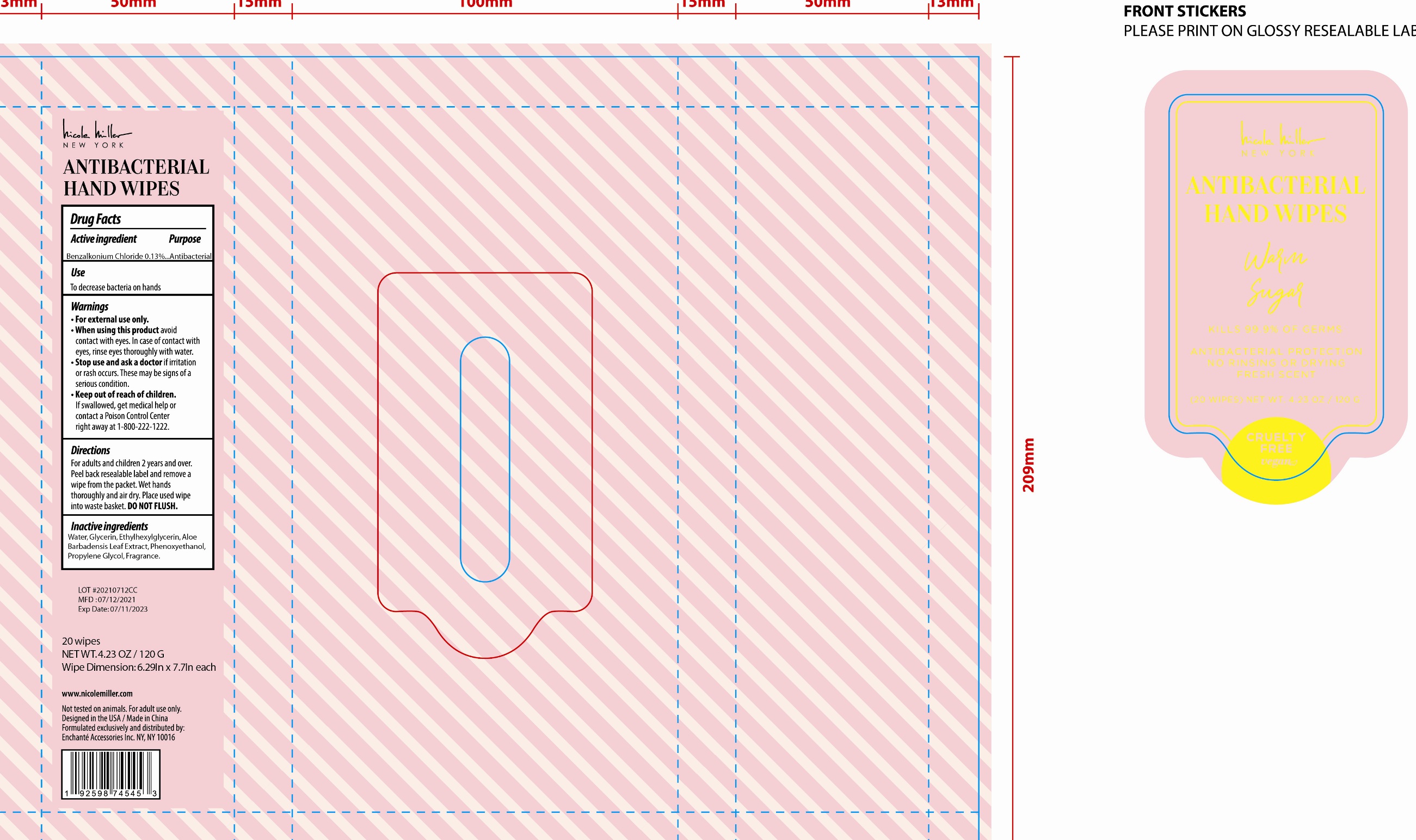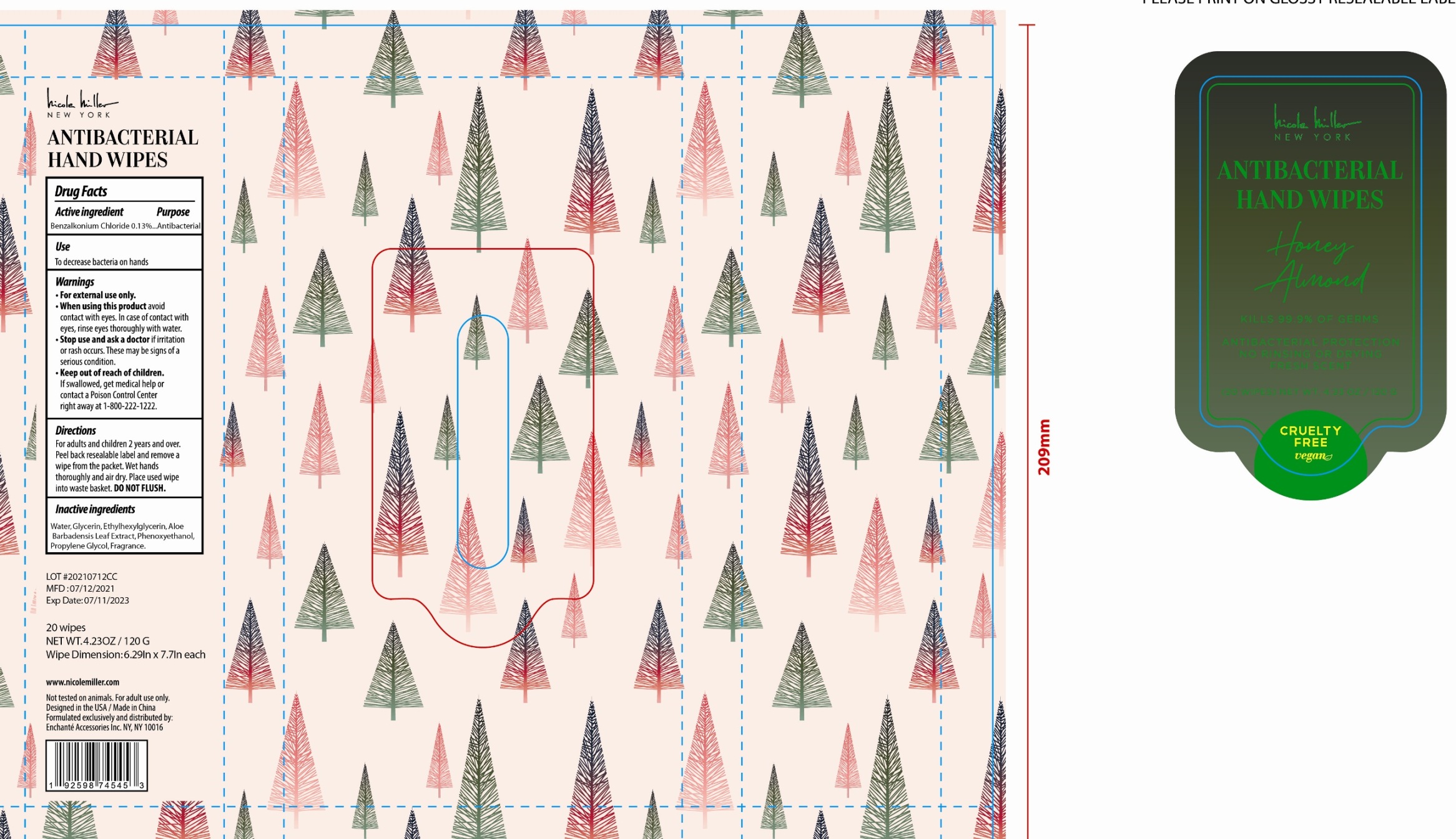 DRUG LABEL: nicole miller NEW YORK ANTIBACTERIAL HAND WIPES  Coconut Vanilla Warm Sugar Honey Almond 3 PACK
NDC: 50563-452 | Form: KIT | Route: TOPICAL
Manufacturer: ENCHANTE ACCESSORIES INC.
Category: otc | Type: HUMAN OTC DRUG LABEL
Date: 20210702

ACTIVE INGREDIENTS: BENZALKONIUM CHLORIDE 0.13 g/100 mL; BENZALKONIUM CHLORIDE 0.13 g/100 mL; BENZALKONIUM CHLORIDE 0.13 g/100 mL
INACTIVE INGREDIENTS: WATER; GLYCERIN; ETHYLHEXYLGLYCERIN; PHENOXYETHANOL; PROPYLENE GLYCOL; ALOE VERA LEAF; WATER; GLYCERIN; ETHYLHEXYLGLYCERIN; PHENOXYETHANOL; PROPYLENE GLYCOL; ALOE VERA LEAF; WATER; GLYCERIN; ETHYLHEXYLGLYCERIN; PHENOXYETHANOL; PROPYLENE GLYCOL; ALOE VERA LEAF

50563-449/450/451/452 G1XABW14

nicole miller NEW YORK ANTIBACTERIAL HAND WIPES Coconut Vanilla

Active Ingredient

Benzalkonium Chloride 0.13%

Purpose

Antibacterial

Use

■ To decrease bacteria on hands

WARNINGS

For external use only

When using this product avoid contact with eyes. In case of contact with eyes, rinse thoroughly with water

Stop use and ask a doctor if irritation or rash occurs. This may be signs of a serious condition

Keep out of reach of children. If swallowed, get medical help or contact a Poison Control Center right away at 1-800-222-1222

Directions

For adults and children two years and over

Peel over resealable label and remove a wipe from the packet.

Wet hands thoroughly and air dry.

Place used wipes into waste basket. Do not flush.

Inactive ingredients

Water, Glycerin, Ethylhexylglycerin, Aloe Barbadensis Leaf Extract, Phenoxyethanol, Propylene Glycol, Fragrance

nicole miller NEW YORK ANTIBACTERIAL HAND WIPES Warm Sugar

Active Ingredient

Benzalkonium Chloride 0.13%

Purpose

Antibacterial

Uses

■ To decrease bacteria on hands

Warnings

For external use only

When using this product avoid contact with eyes. In case of contact with eyes, rinse thoroughly with water

Stop use and ask a doctor if irritation or rash occurs. This may be signs of a serious condition

Keep out of reach of children. If swallowed, get medical help or contact a Poison Control Center right away at 1-800-222-1222

Directions

For adults and children two years and over

Peel over resealable label and remove a wipe from the packet.

Wet hands thoroughly and air dry.

Place used wipes into waste basket. Do not flush.

Inactive Ingredients

Water, Glycerin, Ethylhexylglycerin, Aloe Barbadensis Leaf Extract, Phenoxyethanol, Propylene Glycol, Fragrance

nicole miller NEW YORK ANTIBACTERIAL HAND WIPES Honey Almond

Active Ingredient

Benzalkonium Chloride 0.13%

Purpose

Antibacterial

Uses

■ To decrease bacteria on hands

Warnings

For external use only

When using this product avoid contact with eyes. In case of contact with eyes, rinse thoroughly with water

Stop use and ask a doctor if irritation or rash occurs. This may be signs of a serious condition

Keep out of reach of children. If swallowed, get medical help or contact a Poison Control Center right away at 1-800-222-1222

Directions

For adults and children two years and over

Peel over resealable label and remove a wipe from the packet.

Wet hands thoroughly and air dry.

Place used wipes into waste basket. Do not flush.

Inactive Ingredients

Water, Glycerin, Ethylhexylglycerin, Aloe Barbadensis Leaf Extract, Phenoxyethanol, Propylene Glycol, Fragrance